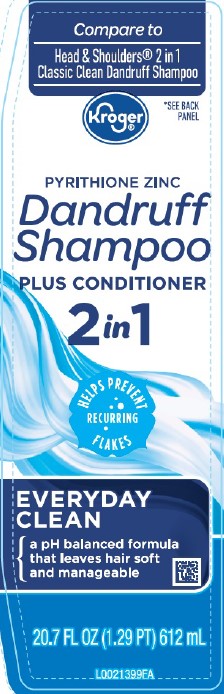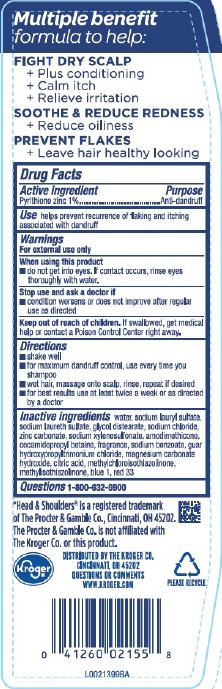 DRUG LABEL: Everyday Clean
NDC: 30142-311 | Form: SHAMPOO
Manufacturer: The Kroger Co.
Category: otc | Type: HUMAN OTC DRUG LABEL
Date: 20260227

ACTIVE INGREDIENTS: PYRITHIONE ZINC 10 mg/1 mL
INACTIVE INGREDIENTS: WATER; SODIUM LAURYL SULFATE; SODIUM LAURETH SULFATE; GLYCOL DISTEARATE; SODIUM CHLORIDE; ZINC CARBONATE; SODIUM XYLENESULFONATE; AMODIMETHICONE (800 CST); COCAMIDOPROPYL BETAINE; SODIUM BENZOATE; GUAR HYDROXYPROPYLTRIMONIUM CHLORIDE (1.7 SUBSTITUENTS PER SACCHARIDE); MAGNESIUM CARBONATE HYDROXIDE; CITRIC ACID MONOHYDRATE; METHYLCHLOROISOTHIAZOLINONE; METHYLISOTHIAZOLINONE; FD&C BLUE NO. 1; D&C RED NO. 33

Kroger 311.007/AK-AN
Dandruff Shampoo, Everyday Clean 2 in 1

Claims

Multiple benefit formula to help:

FIGHT DRY SCALP

+ Plus conditioning

+ Calm itch

+ Relieve irritation

SOOTHE & REDUCE REDNESS

+ Reduce oiliness

PREVENT FLAKES

+ Leaves hair healthy looking

Active ingredient

Pyrithione zinc 1%

Purpose

Anti-dandruff

Use

helps prevent recurrence of flaking and itching associated with dandruff

Warnings

For external use only

When using this product

- do not get into eyes. If contact occurs, rinse eyes thoroughly with water.

Stop use and ask a doctor if

- condition worsens or does not improve after regular use as directed

Keep out of reach of children.

If swallowed, get medical help or contact a Poison Control Center right away.

Directions

- shake well
- for maximum dandruff control, use every time you shampoo
- wet hair, massage into scalp, rinse, repeat if desired
- for best results use at least twice a week or as directed by a doctor

inactive ingredients

water, sodium lauryl sulfate, sodium laureth sulfate, glycol distearate, sodium chloride, zinc carbonate, sodium xylenesulfonate, amodimethicone, cocamidopropyl betaine, fragrance, sodium benzoate, guar hydroxypropyltrimonium chloride, magnesium carbonate hydroxide, citric acid, methylchloroisothiazolinone, methylisothiazolinone, blue 1, red 33

Questions

1-800-632-6900

Disclaimer

*Head & Shoulders®is a registered trademark of The Proctor & Gamble Co., Cincinnati, OH 45202.

The Proctor & Gamble Co. is not affiliated with The Kroger Co. or this product.

Adverse reactions

DISTRIBUTED BY THE KROGER CO.

CINCINNATI, OHIO 45202

QUESTIONS OR COMMENTS

WWW.KROGER.COM

PLEASE RECYCLE

Principal display panel

Compare to Head & Shoulders®2 in 1 Classic Clean Dandruff Shampoo

*SEE BACK PANEL

Kroger®

PYRITHIONE Zinc

Dandruff Shampoo

PLUS CONDITIONER 2 IN 1

HELPS PREVENT REOCCURRING FLAKES

EVERYDAY CLEAN

A pH balanced formula that leaves hair soft and manageable

20.7 FL OZ (1.29 PT) 612 mL